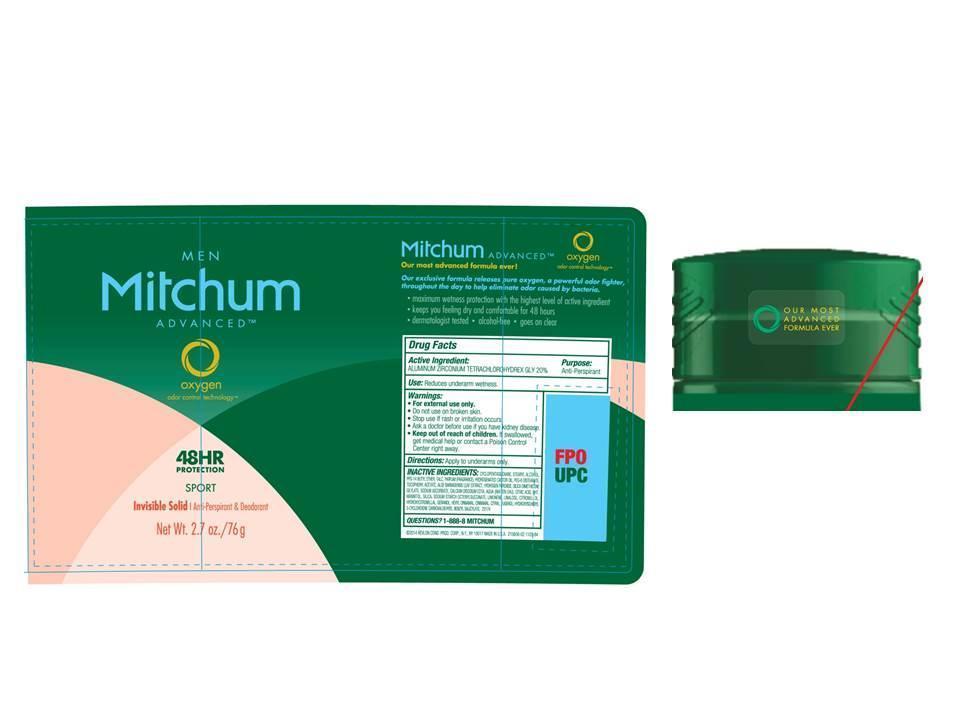 DRUG LABEL: Womens Mitchum Advanced Invisible Antiperspirant Deodorant
NDC: 10967-590 | Form: STICK
Manufacturer: Revlon Consumer Products Corp
Category: otc | Type: HUMAN OTC DRUG LABEL
Date: 20140131

ACTIVE INGREDIENTS: ALUMINUM ZIRCONIUM TETRACHLOROHYDREX GLY 0.20 g/1 g
INACTIVE INGREDIENTS: CYCLOMETHICONE 5; STEARYL ALCOHOL; PPG-14 BUTYL ETHER; TALC; PEG-8 DISTEARATE; HYDROGENATED CASTOR OIL; .ALPHA.-TOCOPHEROL ACETATE; ALOE VERA LEAF; HYDROGEN PEROXIDE; SODIUM ASCORBATE; EDETATE CALCIUM DISODIUM ANHYDROUS; WATER; CITRIC ACID MONOHYDRATE; BUTYLATED HYDROXYTOLUENE; MANNITOL; HYDRATED SILICA; LIMONENE, (+)-; LINALOOL, (+)-; CITRONELLAL; HYDROXYCITRONELLAL; GERANIOL; .ALPHA.-HEXYLCINNAMALDEHYDE; CINNAMALDEHYDE; CITRAL; BENZYL BENZOATE; EUGENOL; HYDROXYISOHEXYL 3-CYCLOHEXENE CARBOXALDEHYDE; BENZYL SALICYLATE; COUMARIN

Mens Mitchum Advanced Invisible Solid Antiperspirant Deodorant (Sport)- 2.7 oz.

Drug Facts Active Ingredient

Aluminum zirconium tetrachlorohydrex gly 20%

Purpose

Antiperspirant

Use

- Reduces underarm wetness

Warnings:

For external use only.

Do not use on broken skin

Ask a doctor before use if you have kidney disease

Stop use if rash or irriation occurs

Keep out of reach of children.

If swallowed, get medical help or contact a Poison Control Center right away.

Directions

Apply to underarms only.

Inactive Ingredients

cyclopentasiloxane, stearyl alcohol, PPG-14 butyl ether, Talc, parfum (fragrance), PEG-8 distearate, hydrogenated castor oil, tocopheryl acetate, aloe barbadensis leaf extract, hydrogen peroxide, silica dimethicone silylate, sodium ascorbate, calcium disodium edta, aqua ((water) eau), citric acid, bht, mannitol, hydrated silica, sodium starch octenylsuccinate, limonene, linalool, citronellol, hydroxycitronellal, geraniol, hexyl cinnamal, cinnamal, citral, benzyl benzoate, eugenol, hydroxyisohexyl 3-cyclohexene carboxaldehyde. benzyl salicylate, methyl 2-octynoate, coumarin

Questions

1-888-8-MITCHUM